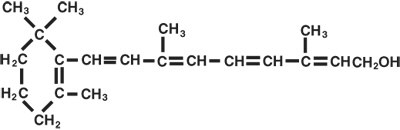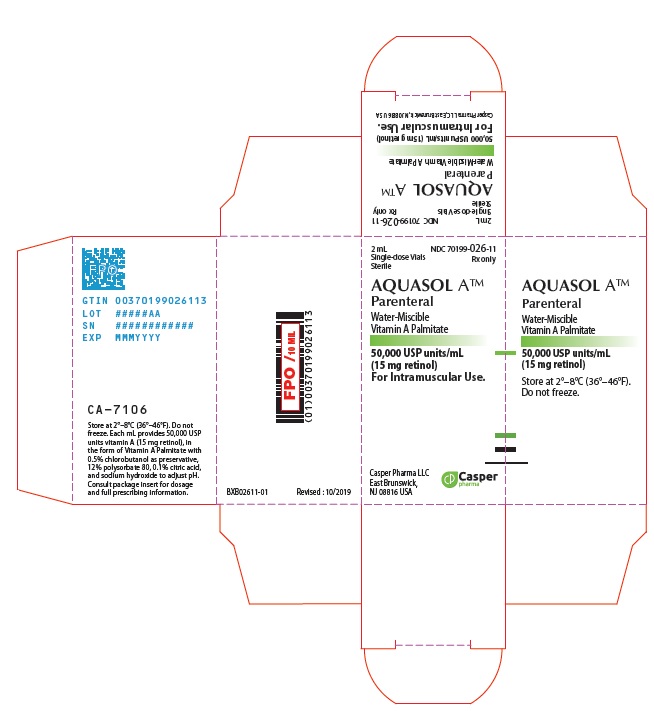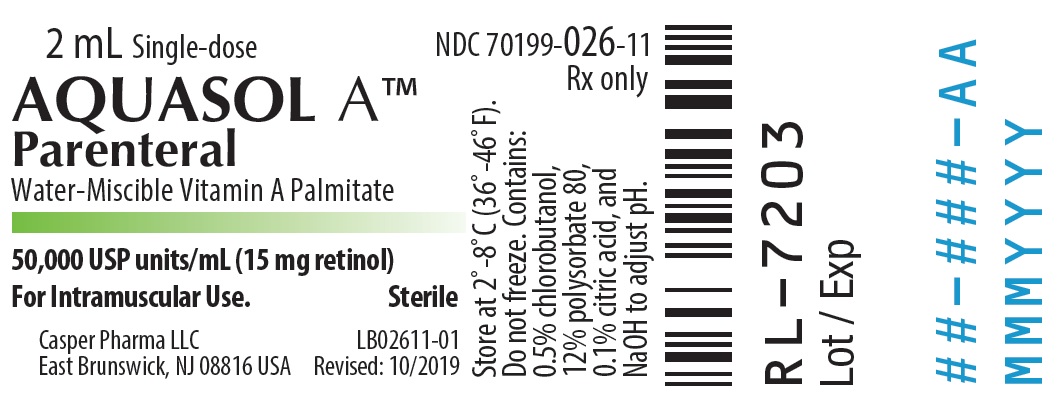 DRUG LABEL: AQUASOL A
NDC: 70199-026 | Form: INJECTION, SOLUTION
Manufacturer: Casper Pharma LLC
Category: prescription | Type: Human Prescription Drug Label
Date: 20200814

ACTIVE INGREDIENTS: VITAMIN A PALMITATE 15 mg/1 mL
INACTIVE INGREDIENTS: CHLOROBUTANOL; POLYSORBATE 80; CITRIC ACID MONOHYDRATE; SODIUM HYDROXIDE

AQUASOL ATM Parenteral

water-miscible vitamin A Palmitate
50,000 USP Units (15 mg retinol/mL) Rx only

THIS IS A STERILE PRODUCT FOR INTRAMUSCULAR INJECTION

DESCRIPTION

AQUASOL ATM Parenteral (water-miscible vitamin A Palmitate) provides 50,000 USP Units of vitamin A per mL as retinol (C20H30O) in the form of vitamin A palmitate, a light yellow to amber oil. Contains 0.5% chlorobutanol as preservative; 12% polysorbate 80, 0.1% citric acid, and sodium hydroxide to adjust pH. The structural formula of retinol is:

Ordinarily oil-soluble, the vitamin A in this product has been water solubilized by special processing* and is available in a water solution for intramuscular injection.

One USP Unit is equivalent to one international unit (IU) and to 0.3 mcg of retinol or 0.6 mcg of betacarotene.

CLINICAL PHARMACOLOGY

Beta-carotene, retinol, and retinal have effective and reliable vitamin A activity. Retinal and retinol are in chemical equilibrium in the body and have equivalent antixerophthalmic activity. Retinal combines with the rod pigment, opsin, in the retina to form rhodopsin, necessary for visual dark adaptation. Vitamin A prevents retardation of growth and preserves the epithelial cells' integrity. Normal adult liver storage is sufficient to satisfy two years' requirements of vitamin A.

Vitamin A is readily absorbed from the gastrointestinal tract, where the biosynthesis of vitamin A from beta-carotene takes place. Vitamin A absorption requires bile salts, pancreatic lipase, and dietary fat. It is transported in the blood to the liver by the chylomicron fraction of the lymph. Vitamin A is stored in Kupffer cells of the liver mainly as the palmitate. Normal serum vitamin A is 80–300 Units per 100 mL (plasma range is 30–70 mcg per dl) and for carotenoids 270–753 Units per 100 mL. The normal adult liver contains approximately 100 to 300 micrograms per gram, mostly as retinol palmitate.

*Oil-soluble vitamin A water solubilized with polysorbate 80.

INDICATIONS

Vitamin A injection is effective for the treatment of vitamin A deficiency.

The parenteral administration is indicated when the oral administration is not feasible as in anorexia, nausea, vomiting, pre- and postoperative conditions, or it is not available as in the "Malabsorption Syndrome" with accompanying steatorrhea.

Pediatric Use: Vitamin A treatment for deficiency states has been recognized as an especially effective and important therapy in the pediatric population.

Vitamin A supplementation for deficiency states in this population has been addressed by the Committee on Clinical Practice Issues of the American Society for Clinical Nutrition, by the American Society for Parenteral and Enteral Nutrition, and by the World Health Organization.

CONTRAINDICATIONS

The intravenous administration. Hypervitaminosis A. Sensitivity to any of the ingredients in this preparation.

Use in Pregnancy: Safety of amounts exceeding 6,000 Units of vitamin A daily during pregnancy has not been established at this time. The use of vitamin A in excess of the recommended dietary allowance may cause fetal harm when administered to a pregnant woman. Animal reproduction studies have shown fetal abnormalities associated with overdosage in several species. Malformations of the central nervous system, the eye, the palate, and the urogenital tract are recorded. Vitamin A in excess of the recommended dietary allowance is contraindicated in women who are or may become pregnant. If vitamin A is used during pregnancy, or if the patient becomes pregnant while taking vitamin A, the patient should be apprised of the potential hazard to the fetus.

WARNINGS

Avoid overdosage. Keep out of the reach of children.

Pediatric Use: Polysorbates have been associated with E-Ferol syndrome (thrombocytopenia, renal dysfunction, hepatomegaly, cholestasis, ascites, hypotension and metabolic acidosis) in low birthweight infants.

PRECAUTIONS

General: Protect from light. Prolonged daily dose administration over 25,000 Units vitamin A should be under close supervision. Blood level assays are not a direct measure of liver storage. Liver storage should be adequate before discontinuing therapy. Single vitamin A deficiency is rare. Multiple vitamin deficiency is expected in any dietary deficiency.

Drug Interactions: Women on oral contraceptives have shown a significant increase in plasma vitamin A levels.

Carcinogenesis: There are no studies that show that administration of vitamin A will cause or prevent cancer.

Pregnancy:

See CONTRAINDICATIONS section.

Nursing Mothers: The U.S. Recommended Daily Allowance (RDA) of vitamin A (5,000 Units) is recommended for nursing mothers.

ADVERSE REACTIONS

See OVERDOSAGE section. Anaphylactic shock and death have been reported using the intravenous route. Allergic reactions have been reported rarely with administration of AQUASOL ATM Parenteral including one case of an anaphylactoid type reaction.

OVERDOSAGE

The following amounts have been found to be toxic orally. Toxicity manifestations depend on the age, dosage, size, and duration of administration.

Acute toxicity — single dose (25,000 Units/kg body weight)
Infant: 350,000 Units
Adult: Over 2 million Units

Chronic toxicity (4,000 Units/kg body weight for 6 to 15 months)
Infants 3 to 6 months old: 18,500 Units (water dispersed)/day for 1 to 3 months.
Adult: 1 million Units daily for three days; 50,000 Units daily for longer than 18 months; 500,000 Units daily for two months.

Hypervitaminosis A Syndrome:

1. General manifestations:
  Fatigue, malaise, lethargy, abdominal discomfort, anorexia, and vomiting.
2. Specific manifestations:
a. Skeletal: hepatotoxicity, hard tender cortical thickening over the radius and tibia, migratory arthralgia, slow growth, and premature closure of the epiphysis leading to arrested bone growth in children.
  b. Central Nervous System: irritability, headache, and increased intracranial pressure as manifested by bulging fontanels, papilledema, and exophthalmos.
  c. Dermatologic: fissures of the lips, drying and cracking of the skin, alopecia, scaling, massive desquamation, and increased pigmentation.
  d. Systemic: hypomenorrhea, hepatosplenomegaly, hepatotoxicity, jaundice, leukopenia, vitamin A plasma level over 1,200 Units/100 mL.

The treatment of hypervitaminosis A consists of immediate withdrawal of the vitamin along with symptomatic and supportive treatment.

DOSAGE AND ADMINISTRATION

For intramuscular use.

I. Adults
  100,000 Units daily for three days followed by 50,000 Units daily for two weeks.
II. Pediatric patients 1 to 8 years old
  17,500 to 35,000 Units daily for 10 days.
III. Infants
  7,500 to 15,000 Units daily for 10 days.

Follow-up therapy with an oral therapeutic multivitamin preparation, containing 10,000 to 20,000 Units vitamin A for adults and for pediatric patients over 8 years old, and 5,000 to 10,000 Units for infants and other pediatric patients under 8 years old, is recommended daily for two months. Low birth-weight infants may require additional vitamin A though the exact dosing in these pediatric patients has not been established. In malabsorption, the parenteral route must be used for an equivalent preparation.

Poor dietary habits should be corrected and an abundant and well-balanced dietary intake should be prescribed.

HOW SUPPLIED

AQUASOL ATM Parenteral (water-miscible vitamin A Palmitate) is available as:

Unit of Sale | Concentration | Each
NDC 70199-026-11 Carton of 1 | 50,000 USP units/mL (15 mg retinol/mL) | NDC 70199-026-11 2 mL Single-dose vial

Store at 2–8°C (36–46°F). Do not freeze.
PIB02611-01
Revised:10/2019

PRINCIPAL DISPLAY PANEL - 2 mL Vial Label

2 mL Single-dose
Rx only
NDC 70199-026-11

AQUASOL A™
Parenteral
Water-Miscible Vitamin A Palmitate

50,000 USP units/mL (15 mg retinol)
For Intramuscular Use.
Sterile

PRINCIPAL DISPLAY PANEL - 2 mL Vial Carton

2 mL
Single-dose Vials
Sterile

NDC 70199-026-11
Rx only

AQUASOL A™
Parenteral
Water-Miscible
Vitamin A Palmitate

50,000 USP units/mL
(15 mg retinol)
For Intramuscular Use.